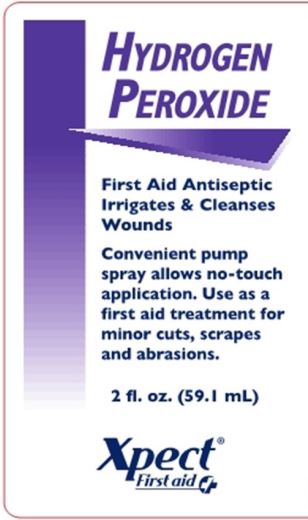 DRUG LABEL: Xpect Hydrogen Peroxide
NDC: 42961-216 | Form: Spray
Manufacturer: Cintas Corporation
Category: otc | Type: HUMAN OTC DRUG LABEL
Date: 20250923

ACTIVE INGREDIENTS: HYDROGEN PEROXIDE 3 mL/100 mL
INACTIVE INGREDIENTS: WATER

Xpect Hydrogen Peroxide

Active ingredients

Hydrogen Peroxide topical solution U.S.P. 3%

Purpose

First Aid Antiseptic

Uses

first aid to help prevent infection in minor cuts, scrapes and burns

Warnings

For external use only

Do not use

- in the eyes or apply over large areas of the body

- longer than 1 week unless directed by a doctor

Ask a doctor before use if you have

- deep or puncture wounds
- animal bites
- serious burns

Stop use and ask a doctor if

- condition persists or gets worse

Keep out of reach of children.

If swallowed, get medical help or contact Poison Control Center right away.

Directions

- clean the affected area
- spray a small amount 1 to 3 times daily
- may be covered with a sterile bandage.
- if bandaged, let dry first

Other information

- store at room temperature

Inactive Ingredients

- purified water

Questions?

1-877-973-2811 M-F 8am-5pm

Package Principal Display Panel

HYDROGEN

PEROXIDE

First Aid Antiseptic

Irrigates & Cleanses Wounds

Convenient pump spray allows no-touch application. Use as a first aid treatment for minor cuts, scrapes and abrasions.

2 fl. oz. (59.1 mL)

Xpect® First aid